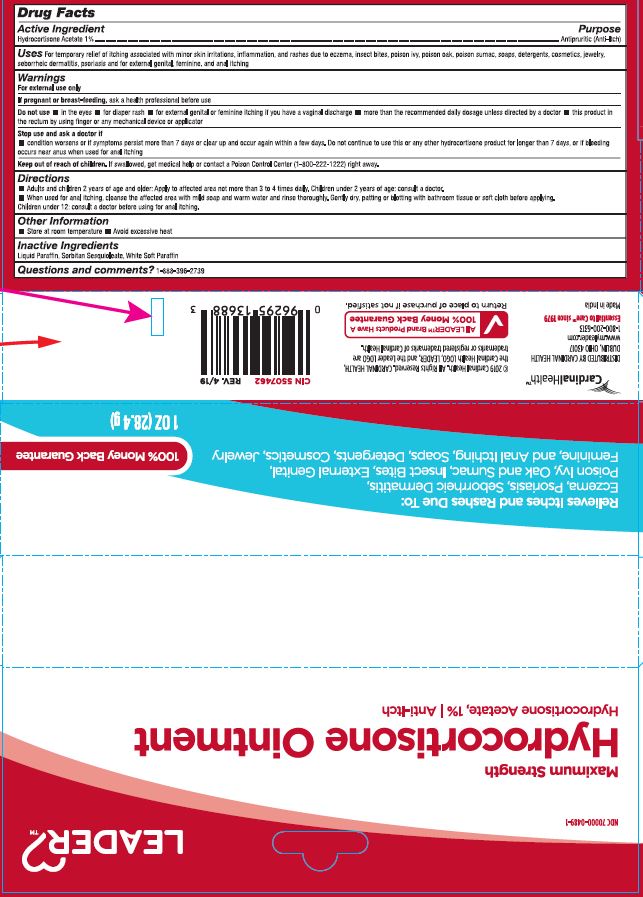 DRUG LABEL: Hydrocortisone
NDC: 70000-0489 | Form: OINTMENT
Manufacturer: Cardinal Health
Category: otc | Type: HUMAN OTC DRUG LABEL
Date: 20251125

ACTIVE INGREDIENTS: HYDROCORTISONE ACETATE 1 g/100 g
INACTIVE INGREDIENTS: MINERAL OIL; SORBITAN SESQUIOLEATE; PETROLATUM

CR-1138 Hydrocortisone Acetate 1% Ointment, NDC 70000-0489-1

Active Ingredient

Hydrocortisone Acetate

Purpose

Antipruritic (Anti-Itch)

Uses

For temporary relief of itching associated with minor skin irritations, inflammation, and rashes due to eczema, insect bites, poison ivy, poison oak, poison sumak, soaps, detergents, cosmetics, jewelry, seborrheic dermatitis, psoriasis and for external genital, feminine and anal itching

Warnings

For external use only

If pregnant or breast-feeding,

ask a health professional before use

Do not use

- in the eyes
- for diaper rash
- for external genital or feminine itching if you have a vaginal discharge
- more than the recommended daily dosage unless directed by a doctor
- this product in the rectum by using finger or any mechanical device

Stop use and ask a doctor if

condition worsens or if symptoms persist more than 7 days or clear up and occur again within a few days. Do not continue to use this or any other hydrocortisone product for longer than 7 days, or if bleeding occurs near anus when used for anal itching

KEEP OUT OF REACH OF CHILDREN

If swallowed, get medical help or contact a poison control center (1-800-222-1222) right away.

Directions

- Adults and children 2 years of age and older: Apply to affected area not more than 3 to 4 times daily. Children under 2 years of age: consult a doctor.
- When used for anal itching, cleanse the affected area with mild soap and warm water and rinse thoroughly. Gently dry, patting or blotting with bathroom tissue or soft cloth before applying. Children under 12: consult a doctor before using for anal itching.

Other Information

- Store at room temperature
- Avoid excessive heat

Inactive Ingredients

Liquid Paraffin, Sorbitan Sesquioleate, White Soft Paraffin

Questions and comments?

1-888-396-2739